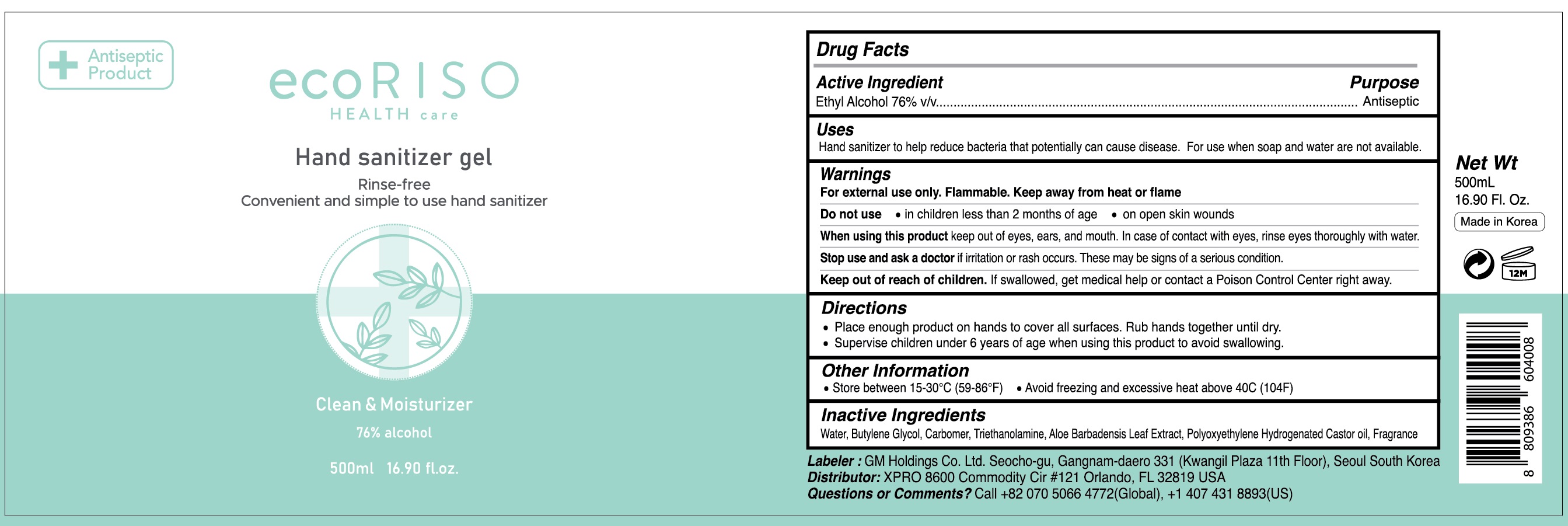 DRUG LABEL: Ecoriso Health Care Hand Sanitizer
NDC: 69278-120 | Form: GEL
Manufacturer: GM Holdings Co., Ltd
Category: otc | Type: HUMAN OTC DRUG LABEL
Date: 20200630

ACTIVE INGREDIENTS: ALCOHOL 380 mL/500 mL
INACTIVE INGREDIENTS: Water; Butylene Glycol; CARBOMER HOMOPOLYMER, UNSPECIFIED TYPE; TROLAMINE; ALOE VERA LEAF

Drug Facts

ACTIVE INGREDIENT

Ethyl Alcohol 76% v/v

INACTIVE INGREDIENTS

Water, Butylene Glycol, Carbomer, Triethanolamine, Aloe Barbadensis Leaf Extract, Polyoxyethylene Hydrogenated Castor oil, Fragrance

PURPOSE

Antiseptic

WARNINGS

For external use only. Flammable. Keep away from heat or flame

Do not use
• in children less than 2 months of age
• on open skin wounds

When using this product keep out of eyes, ears, and mouth. In case of contact with eyes, rinse eyes thoroughly with water.

Stop use and ask a doctor if irritation or rash occurs. These may be signs of a serious condition.

KEEP OUT OF REACH OF CHILDREN

If swallowed, get medical help or contact a Poison Control Center right away.

Uses:

Hand sanitizer to help reduce bacteria that potentially can cause disease.

For use when soap and water are not available

Directions

• Place enough product on hands to cover all surfaces. Rub hands together until dry.
• Supervise children under 6 years of age when using this product to avoid swallowing.

Other information

• Store between 15-30C (59-86F)
• Avoid freezing and excessive heat above 40C (104F)